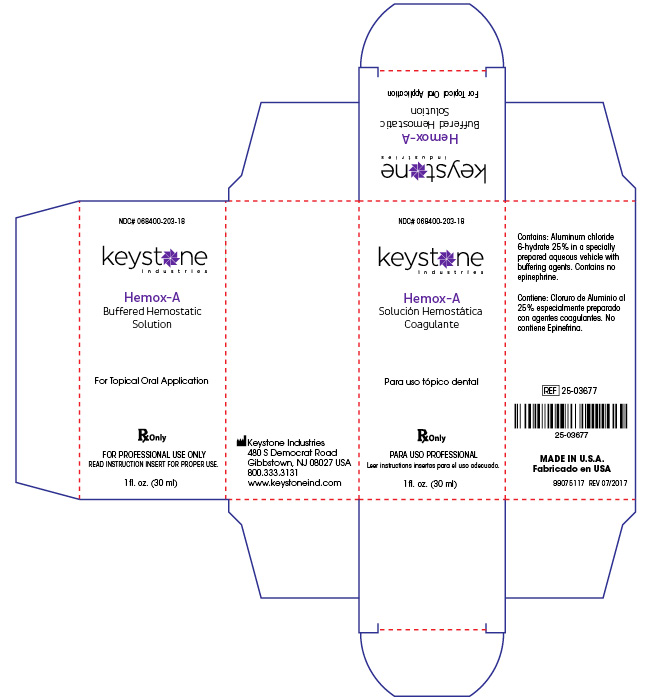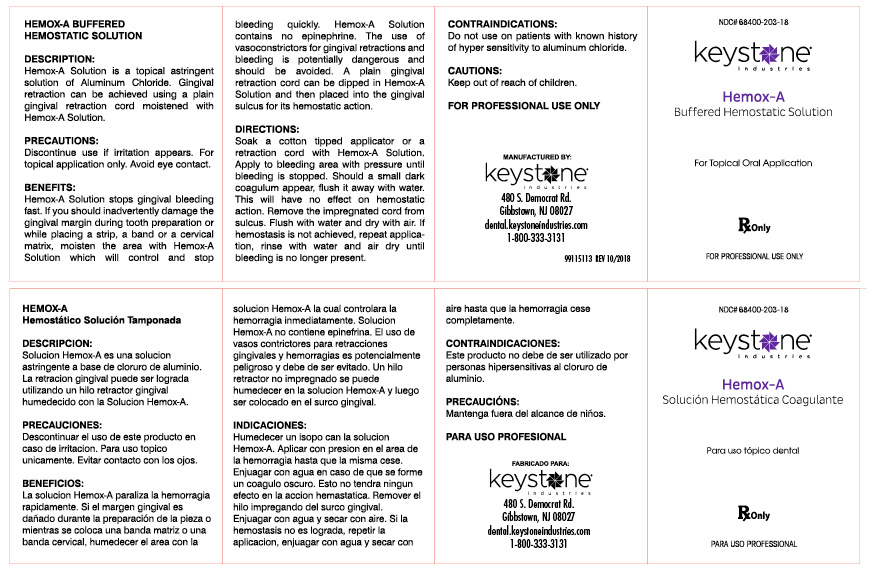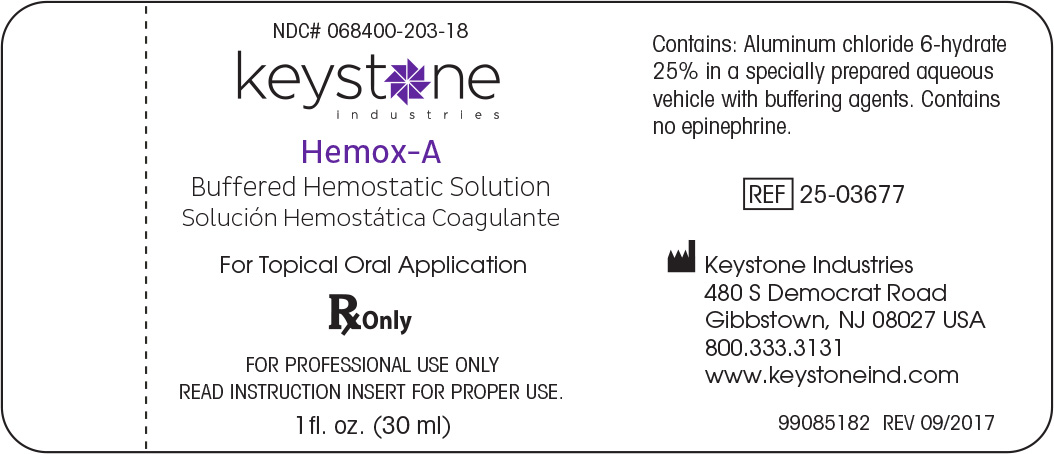 DRUG LABEL: Hemox A
NDC: 68400-203 | Form: SOLUTION
Manufacturer: Mycone Dental Supply Co., Inc DBA Keystone Industries and Deepak Products Inc.
Category: prescription | Type: HUMAN PRESCRIPTION DRUG LABEL
Date: 20220120

ACTIVE INGREDIENTS: ALUMINUM CHLORIDE 7500 mg/30 mL
INACTIVE INGREDIENTS: WATER; PROPYLENE GLYCOL; POTASSIUM CHLORIDE; DMDM HYDANTOIN

DESCRIPTION:

Hemox-A Solution is a topical astringent solution of Aluminum Chloride. Gingival retraction can be achieved using a plain gingival retraction cord moistened with Hemox-A Solution.

PRECAUTIONS:

Discontinue use if irritation appears. For topical application only. Avoid eye contact.

BENEFITS:

Hemox-A Solution stops gingival bleeding fast. If you should inadvertantly damage the gingival margin during tooth preparation or while placing a strip, band or a cerival matrix, moisten the area with Hemox-A Solution which will control and stop bleeding quickly. Hemox-A Solution contains no epinephrine. The use of vasoconstrictors for gingival retractions and bleeding is potentially dangerous and should be avoided. A plain gingival retraction cord can be dipped in Hemox-A Solution and then placed into the gingival sulcus for its hemostatic action.

DIRECTIONS:

Soak a cotton tipped applicator or a retraction cord with Hemox-A Solution. Apply to bleeding area with pressure until bleeding is stopped. Should a small dark coagulum appear, flush it away with water. This will have no effect on hemostatic action. Remove the impregnated cord from sulcus. Flush with water and dry with air. If hemostatis is not achieved, repeat application, rinse with water and air dry until bleeding is no longer present.

CONTRAINDICATIONS:

Do not use on patients with known history of hypersensitivity to aluminum chloride.

CAUTIONS:

Keep out of reach of children.

FOR PROFESSIONAL USE ONLY